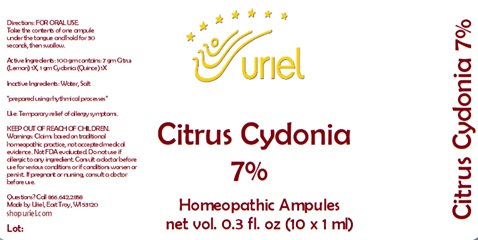 DRUG LABEL: Citrus Cydonia 7
NDC: 48951-3106 | Form: LIQUID
Manufacturer: Uriel Pharmacy Inc.
Category: homeopathic | Type: HUMAN OTC DRUG LABEL
Date: 20240327

ACTIVE INGREDIENTS: LEMON 1 [hp_X]/1 mL; QUINCE 1 [hp_X]/1 mL
INACTIVE INGREDIENTS: WATER; SODIUM CHLORIDE

Citrus Cydonia 7

INDICATIONS AND USAGE

Directions: FOR ORAL USE.

DOSAGE AND ADMINISTRATION

Take the contents of one ampule under the tongue and hold for 30 seconds, then swallow.

ACTIVE INGREDIENT

Active Ingredients: 100 gm contains: 7 gm Citrus (Lemon) 1X, 1 gm Cydonia (Quince) 1X

Inactive Ingredients: Water, Salt

prepared using rhythmical processes

PURPOSE

Use: Temporary relief of allergy symptoms.

KEEP OUT OF REACH OF CHILDREN.

WARNINGS

Warnings: Claims based on traditional homeopathic practice, not accepted medical evidence. Not FDA evaluated. Do not use if allergic to any ingredient. Consult a doctor before use for serious conditions or if conditions worsen or persist. If pregnant or nursing, consult a doctor before use.

QUESTIONS

Questions? Call 866.642.2858 Made by Uriel, East Troy, WI 53120 shopuriel.com Lot: